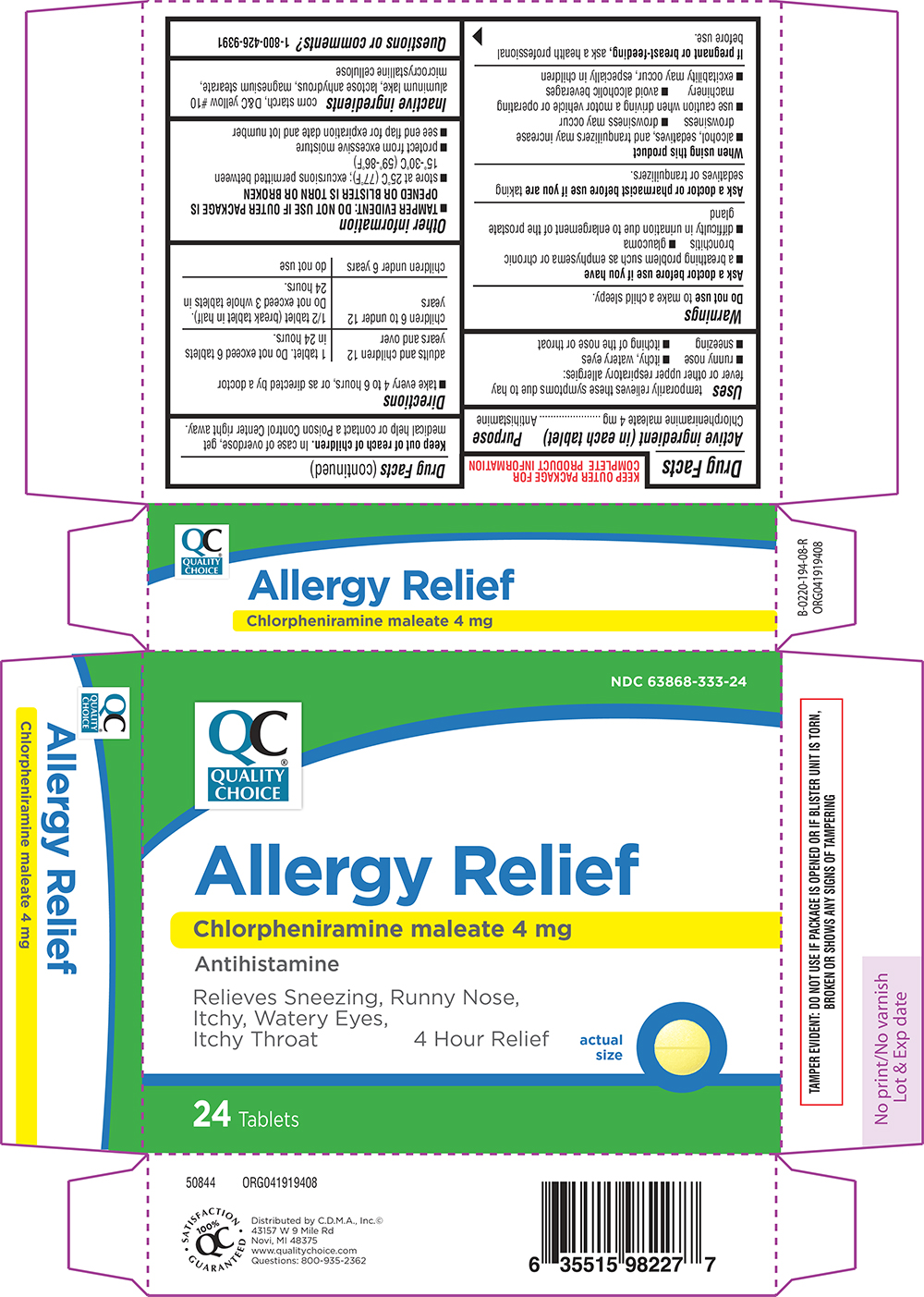 DRUG LABEL: Allergy Relief
NDC: 63868-333 | Form: TABLET
Manufacturer: CHAIN DRUG MARKETING ASSOCIATION INC
Category: otc | Type: HUMAN OTC DRUG LABEL
Date: 20251212

ACTIVE INGREDIENTS: CHLORPHENIRAMINE MALEATE 4 mg/1 1
INACTIVE INGREDIENTS: STARCH, CORN; D&C YELLOW NO. 10 ALUMINUM LAKE; ANHYDROUS LACTOSE; MAGNESIUM STEARATE; MICROCRYSTALLINE CELLULOSE

Quality Choice 44-194-Delisted

Active ingredient (in each tablet)

Chlorpheniramine maleate 4 mg

Purpose

Antihistamine

Uses

temporarily relieves these symptoms due to hay fever or other upper respiratory allergies:

- runny nose
- itchy, watery eyes
- sneezing
- itching of the nose or throat

Warnings

Do not use

to make a child sleepy.

Ask a doctor before use if you have

- a breathing problem such as emphysema or chronic bronchitis
- glaucoma
- difficulty in urination due to enlargement of the prostate gland

Ask a doctor or pharmacist before use if you are

taking sedatives or tranquilizers.

When using this product

- alcohol, sedatives, and tranquilizers may increase drowsiness
- drowsiness may occur
- use caution when driving a motor vehicle or operating machinery
- avoid alcoholic beverages
- excitability may occur, especially in children

If pregnant or breast-feeding,

ask a health professional before use.

Keep out of reach of children.

In case of overdose, get medical help or contact a Poison Control Center right away.

Directions

- take every 4 to 6 hours, or as directed by a doctor

adults and children 12 years and over | 1 tablet. Do not exceed 6 tablets in 24 hours.
children 6 to under 12 years | 1/2 tablet (break tablet in half). Do not exceed 3 whole tablets in 24 hours.
children under 6 years | do not use

Other information

- TAMPER EVIDENT: DO NOT USE IF OUTER PACKAGE IS OPENED OR BLISTER IS TORN OR BROKEN
- store at 25°C (77°F); excursions permitted between 15°-30°C (59°-86°F)
- protect from excessive moisture
- see end flap for expiration date and lot number

Inactive ingredients

corn starch, D&C yellow #10 aluminum lake, lactose anhydrous, magnesium stearate, microcrystalline cellulose

Questions or comments?

1-800-426-9391

Principal display panel

QC®
Quality
Choice

NDC 63868-333-24

Allergy Relief
Chlorpheniramine maleate 4 mg
Antihistamine

Relieves Sneezing, Runny Nose,
Itchy, Watery Eyes,
Itchy Throat

4 Hour Relief

actual
size

24 Tablets

TAMPER EVIDENT: DO NOT USE IF PACKAGE IS OPENED OR IF BLISTER UNIT IS TORN,
BROKEN OR SHOWS ANY SIGNS OF TAMPERING

50844 ORG041919408

Distributed by C.D.M.A., Inc.©
43157 W 9 Mile Rd
Novi, MI 48375
www.qualitychoice.com
Questions: 800-935-2362

Quality Choice 44-194